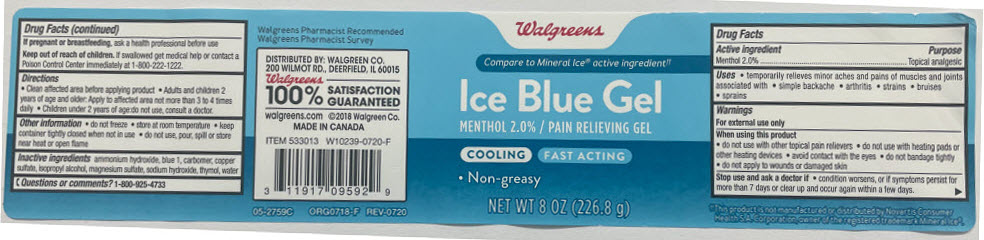 DRUG LABEL: Walgreens Ice Blue Pain Relieving
NDC: 0363-6330 | Form: GEL
Manufacturer: Walgreen Company
Category: otc | Type: HUMAN OTC DRUG LABEL
Date: 20241104

ACTIVE INGREDIENTS: MENTHOL, UNSPECIFIED FORM 20 mg/1 g
INACTIVE INGREDIENTS: AMMONIA; DISODIUM N-ETHYL-N-4-((4-(ETHYL((3-SULFOPHENYL)METHYL)AMINO)PHENYL)(2-SULFOPHENYL)METHYLENE)-2,5-CYCLOHEXADIEN-1-YLIDENE)-3-SULFOBENZENEMETHANAMINIUM; CARBOMER HOMOPOLYMER, UNSPECIFIED TYPE; CUPRIC SULFATE ANHYDROUS; Isopropyl Alcohol; MAGNESIUM SULFATE ANHYDROUS; Sodium Hydroxide; Thymol; Water

Walgreens Ice Blue Gel Pain Relieving Gel
Topical Analgesic

Drug Facts

Active ingredient

Menthol 2.0%

Purpose

Topical Analgesic

Uses

- temporarily relieves minor aches and pains of muscles and joints associated with
  - simple backache
  - arthritis
  - strains
  - bruises
  - sprains

Warnings

For external use only

When using this product

- do not use with other topical pain relievers
- do not use with heating pads or other heating devices
- avoid contact with the eyes
- do not bandage tightly
- do not apply to wounds or damaged skin

Stop use and ask a doctor if

- condition worsens, or if symptoms persist for more than 7 days or clear up and occur again within a few days.

PREGNANCY OR BREAST FEEDING

If pregnant or breastfeeding, ask a health professional before use

Keep out of reach of children. If swallowed, get medical help or contact a Poison Control Center immediately at 1-800-222-1222.

Directions

- Clean affected area before applying product
- adults and children 2 years of age and older: apply to affected area not more than 3 to 4 times daily
- children under 2 years of age: do not use, consult a doctor.

Other information

- do not freeze
- store at room temperature
- keep container tightly closed when not in use
- do not use, pour, spill or store near heat or open flame

Inactive ingredients

ammonium hydroxide, blue 1, carbomer, copper sulfate, isopropyl alcohol, magnesium sulfate, sodium hydroxide, thymol, water.

Questions or comments?

1-800-925-4733

DISTRIBUTED BY: WALGREEN CO.
200 WILMOT RD., DEERFIELD, IL 60015

PRINCIPAL DISPLAY PANEL - 226.8 g Jar Label

Walgreens

Compare to Mineral Ice® active ingredient††

Ice Blue Gel
MENTHOL 2.0% / PAIN RELIEVING GEL

COOLING
FAST ACTING

- Non-greasy

NET WT 8 OZ (226.8 g)